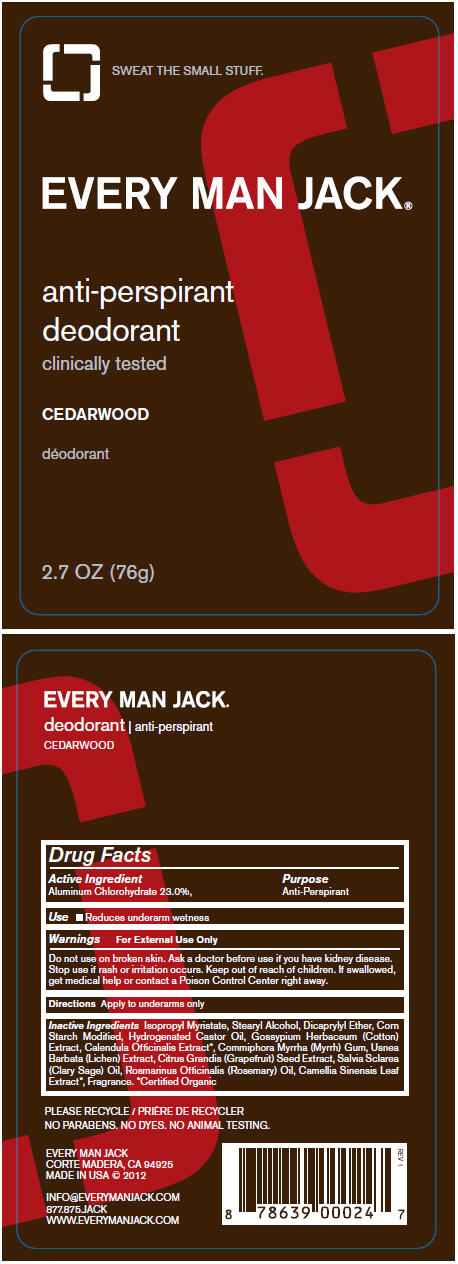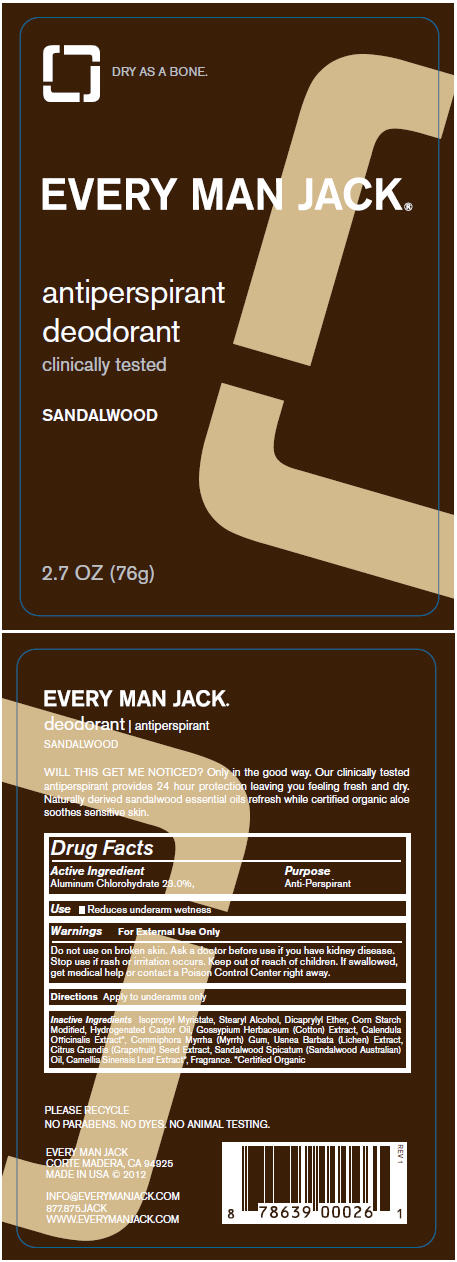 DRUG LABEL: Antiperspirant Cedarwood
NDC: 57934-0103 | Form: STICK
Manufacturer: Every man jack
Category: otc | Type: HUMAN OTC DRUG LABEL
Date: 20130905

ACTIVE INGREDIENTS: Aluminum Chlorohydrate 23 g/100 g
INACTIVE INGREDIENTS: isopropyl myristate; stearyl alcohol; dicaprylyl ether; starch, corn; hydrogenated castor oil; levant cotton seed; calendula officinalis flower; myrrh; usnea barbata; citrus paradisi seed; clary sage oil; rosemary oil; green tea leaf

Antiperspirant Cedarwood

Drug Facts

Active Ingredient

Aluminum Chlorohydrate 23.0%,

Purpose

Anti-Perspirant

Use

- Reduces underarm wetness

Warnings

For External Use Only

Do not use on broken skin.

Ask a doctor before use if you have kidney disease.

Stop use if rash or irritation occurs.

Keep out of reach of children. If swallowed, get medical help or contact a Poison Control Center right away.

Directions

Apply to underarms only

Inactive Ingredients

Isopropyl Myristate, Stearyl Alcohol, Dicaprylyl Ether, Corn Starch Modified, Hydrogenated Castor Oil, Gossypium Herbaceum (Cotton) Extract, Calendula Officinalis Extract [Certified Organic] , Commiphora Myrrha (Myrrh) Gum, Usnea Barbata (Lichen) Extract, Citrus Grandis (Grapefruit) Seed Extract, Salvia Sclarea (Clary Sage) Oil, Rosmarinus Officinalis (Rosemary) Oil, Camellia Sinensis Leaf Extract, Fragrance.

PRINCIPAL DISPLAY PANEL - 76g Tube Label

SWEAT THE SMALL STUFF.

EVERY MAN JACK®

anti-perspirant
deodorant

clinically tested

CEDARWOOD

2.7 OZ (76g)

PRINCIPAL DISPLAY PANEL - 76g Tube Label

DRY AS A BONE.

EVERY MAN JACK®

antiperspirant
deodorant

clinically tested

SANDALWOOD

2.7 OZ (76g)